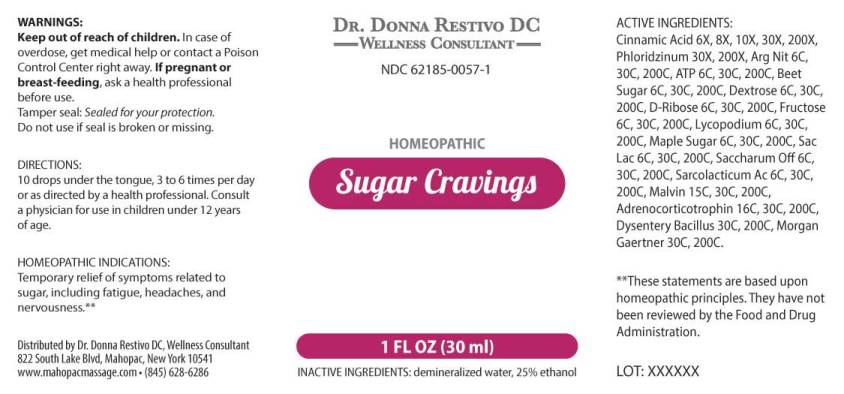 DRUG LABEL: Sugar Cravings
NDC: 62185-0057 | Form: LIQUID
Manufacturer: Dr. Donna Restivo DC
Category: homeopathic | Type: HUMAN OTC DRUG LABEL
Date: 20251021

ACTIVE INGREDIENTS: CINNAMIC ACID 6 [hp_X]/1 mL; PHLORIZIN 30 [hp_X]/1 mL; SILVER NITRATE 6 [hp_C]/1 mL; ADENOSINE TRIPHOSPHATE DISODIUM 6 [hp_C]/1 mL; SUCROSE 6 [hp_C]/1 mL; DEXTROSE, UNSPECIFIED FORM 6 [hp_C]/1 mL; RIBOSE, D- 6 [hp_C]/1 mL; FRUCTOSE 6 [hp_C]/1 mL; LYCOPODIUM CLAVATUM SPORE 6 [hp_C]/1 mL; ACER SACCHARUM SAP 6 [hp_C]/1 mL; LACTOSE, UNSPECIFIED FORM 6 [hp_C]/1 mL; LACTIC ACID, L- 6 [hp_C]/1 mL; MALVIN 15 [hp_C]/1 mL; CORTICOTROPIN 16 [hp_C]/1 mL; SHIGELLA DYSENTERIAE 30 [hp_C]/1 mL; SALMONELLA ENTERICA SUBSP. ENTERICA SEROVAR ENTERITIDIS 30 [hp_C]/1 mL
INACTIVE INGREDIENTS: WATER; ALCOHOL

DRUG FACTS:

ACTIVE INGREDIENTS:

Cinnamic Acid 6X, 8X, 10X, 30X, 200X, Phloridzinum 30X, 200X, Argentum Nitricum 6C, 30C, 200C, Adenosinum Triphosphoricum Dinatrum 6C, 30C, 200C, Beet Sugar 6C, 30C, 200C, Dextrose 6C, 30C, 200C, D-Ribose 6C, 30C, 200C, Fructose 6C, 30C, 200C, Lycopodium Clavatum 6C, 30C, 200C, Maple Sugar 6C, 30C, 200C, Saccharum Lactis 6C, 30C, 200C, Saccharum Officinale 6C, 30C, 200C, Sarcolacticum Acidum 6C, 30C, 200C, Malvin 15C, 30C, 200C, Adrenocorticotrophin 16C 30C, 200C, Dysentery Bacillus 30C, 200C, Morgan Gaertner 30C, 200C.

HOMEOPATHIC INDICATIONS:

Temporary relief of symptoms related to sugar, including fatigue, headaches, and nervousness.**

**These statements are based upon homeopathic principles. They have not been reviewed by the Food and Drug Administration.

WARNINGS:

Keep out of reach of children. In case of overdose, get medical help or contact a Poison Control Center right away.

If pregnant or breast-feeding, ask a health professional before use.

Tamper seal: Sealed for your protection.

Do not use if seal is broken or missing.

Keep out of reach of children. In case of overdose, get medical help or contact a Poison Control Center right away.

DIRECTIONS:

10 drops under the tongue 3 to 6 times per day or as directed by a health professional. Consult a physician for use in children under 12 years of age.

HOMEOPATHIC INDICATIONS:

Temporary relief of symptoms related to sugar, including fatigue, headaches, and nervousness.**

**These statements are based upon homeopathic principles. They have not been reviewed by the Food and Drug Administration.

INACTIVE INGREDIENTS:

demineralized water, 25% ethanol

QUESTIONS:

Distributed by Dr. Donna Restivo DC, Wellness Consultant

822 South Lake Blvd, Mahopac, New York 10541

www.mahopacmassage.com • (845)628-6286

PACKAGE LABEL DISPLAY:

DR. DONNA RESTIVO DC

WELLNESS CONSULTANT

NDC 62185-0057-1

HOMEOPATHIC

Sugar Cravings

1 FL OZ (30 ml)